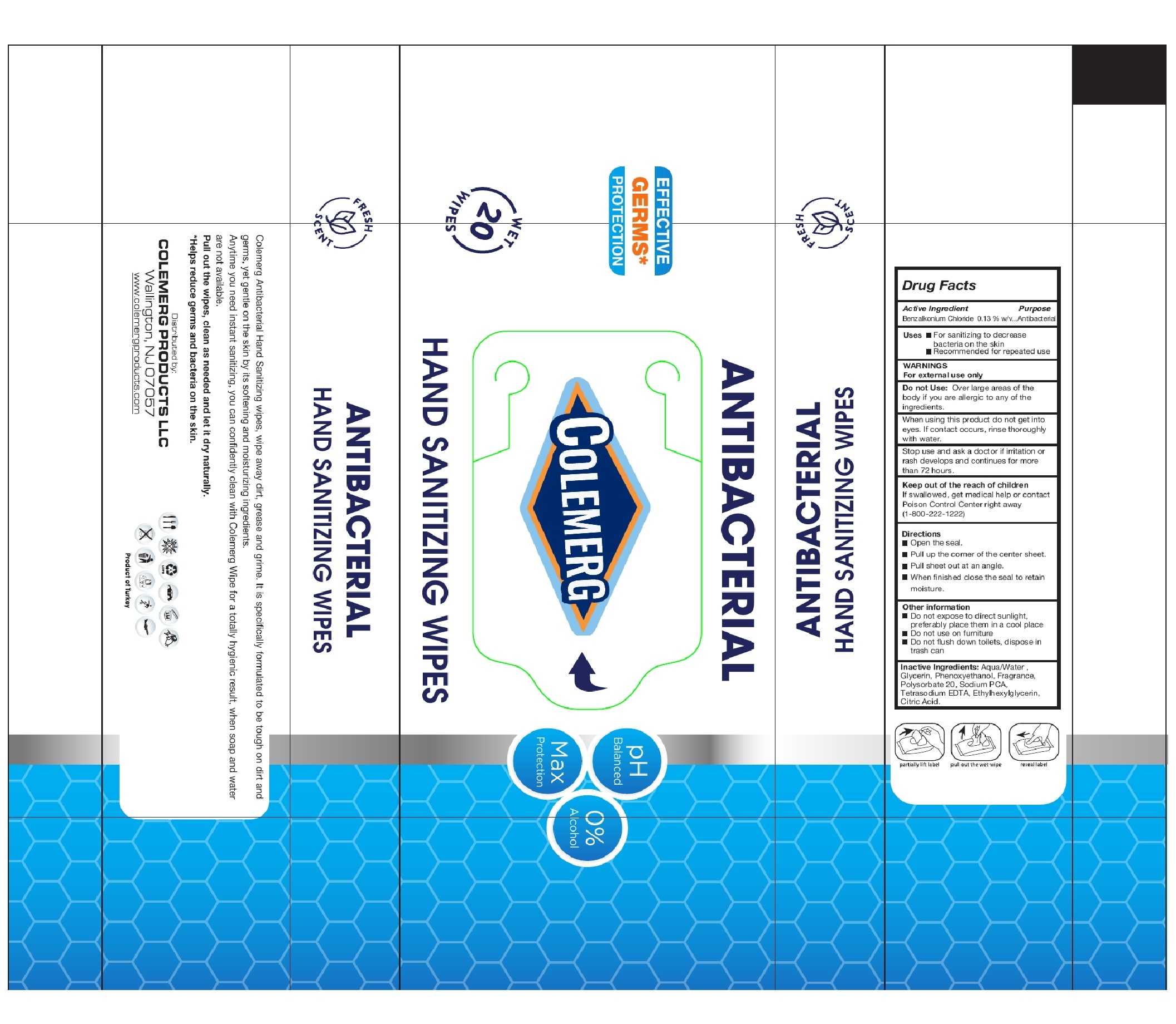 DRUG LABEL: Colemerg Antibacterial Hand Sanitizing Wipes
NDC: 80171-002 | Form: CLOTH
Manufacturer: Colemerg Products LLC
Category: otc | Type: HUMAN OTC DRUG LABEL
Date: 20201111

ACTIVE INGREDIENTS: BENZALKONIUM CHLORIDE 1.3 mg/1 mL
INACTIVE INGREDIENTS: WATER; GLYCERIN; PHENOXYETHANOL; POLYSORBATE 20; SODIUM PYRROLIDONE CARBOXYLATE; EDETATE SODIUM; ETHYLHEXYLGLYCERIN; CITRIC ACID MONOHYDRATE

Colemerg Antibacterial Hand Sanitizing Wipes

Active Ingredient

Benzalkonium Chloride 0.13 % w/v

Purpose

Antibacterial

Uses

- For sanitizing to decrease bacteria on the skin
- Recommended for repeated use

WARNINGS

For external use only

Do not use:

Over large areas of the body if you are allegic to any of the ingredients.

When using this product

do not get into eyes. If contact occurs, rinse thoroughly with water.

Stop use and ask a doctor if

irritation or rash develops and continues for more than 72 hours.

Keep out of reach of children

If swallowed, get medical help or contact Poison Control Center right away (1-800-222-1222)

Directions

- Remove lid and open the seal.
- Pull up the corner of the center sheet, twist it and thread through the dispenser slipt in the lid.
- Pull sheet out at an angle. When finished close lid flap to retain moisure.

Other Information:

- Do not expose to direct sunlight, preferably place them in a cool place
- Do not use on furniture
- Do not flush down toilets, dispose in trash can

Inactive Ingredients:

Aqua/Water, Glycerin, Phenoxyethanol, Parfum/Fragrance, Polysorbate 20, Sodium PCA, Tetrasodium Edta, Ethylhexylglycerin, Citric Acid.